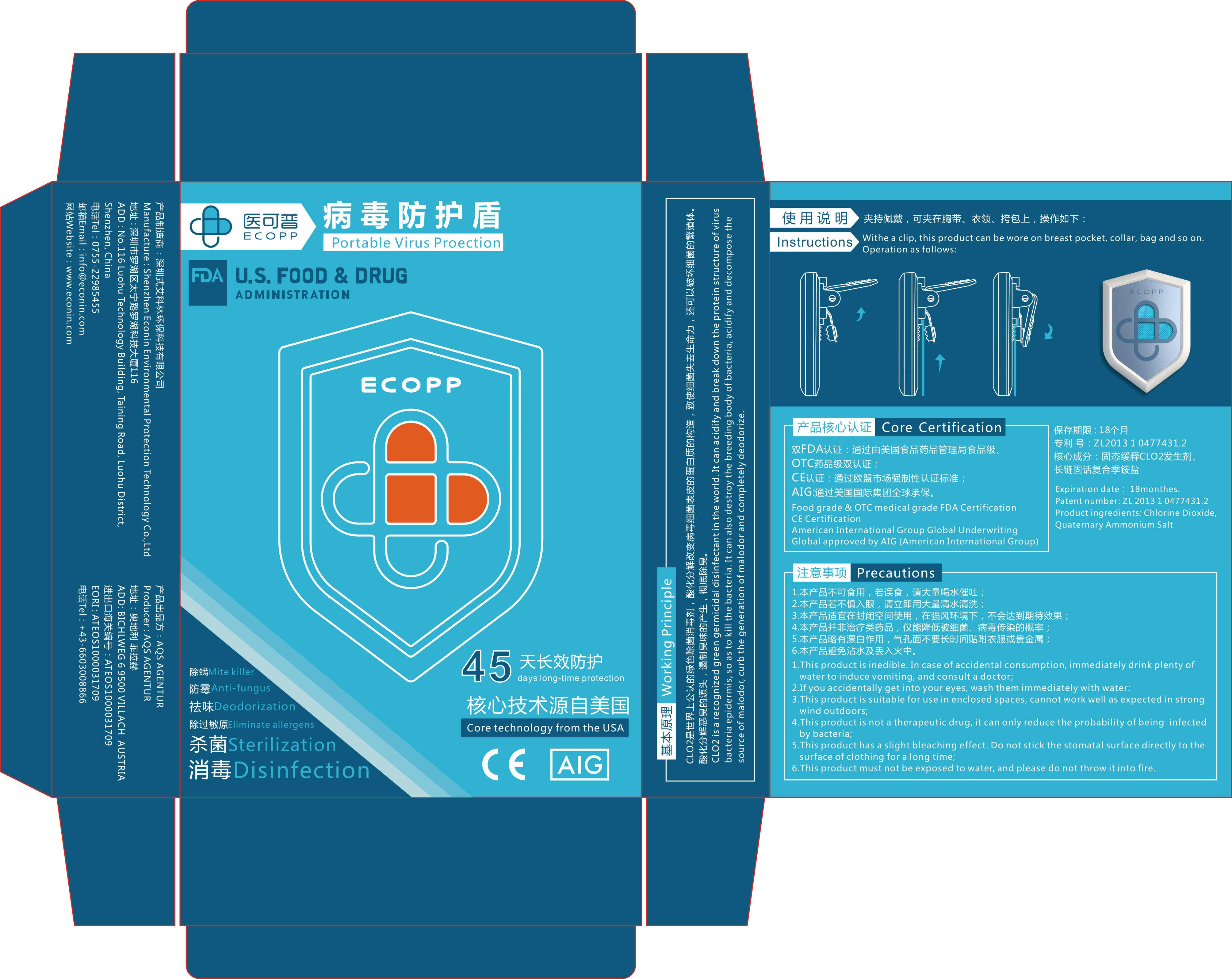 DRUG LABEL: ecopp portable virus proection
NDC: 42134-001 | Form: GRANULE
Manufacturer: Shenzhen Econin Environmental Protection Technology Co., Ltd.
Category: otc | Type: HUMAN OTC DRUG LABEL
Date: 20200328

ACTIVE INGREDIENTS: CHLORINE DIOXIDE 0.595 g/3.5 g; AMMONIUM CHLORIDE 0.007 g/3.5 g
INACTIVE INGREDIENTS: BENZALKONIUM CHLORIDE

DOSAGE AND ADMINISTRATION

This product is suitable for use in enclosed spaces, cannot work well as expected in strong wind outdoors.

INACTIVE INGREDIENT

benzalkonium chloride

WARNINGS

This product has a slight bleaching effect. Do not stick the stomatal surface directly to the surface of clothing for a long time;

This product must not be exposed to water, and please do not throw it into fire.

ACTIVE INGREDIENT

0.18% - 0.22% Behenyl Trimethyl Ammonium Chloride

17% chlorine dioxide

keep out of reach of children

INDICATIONS AND USAGE

This product is inedible. In case of accidental consumption, immediately drink plenty of water to induce vomiting, and consult a doctor.

If you accidentally get into your eyes, wash them immediately with water.

PURPOSE

mite killer

anti-fungus

deodorization

eliminate allergens

sterilizaiton

disinfection